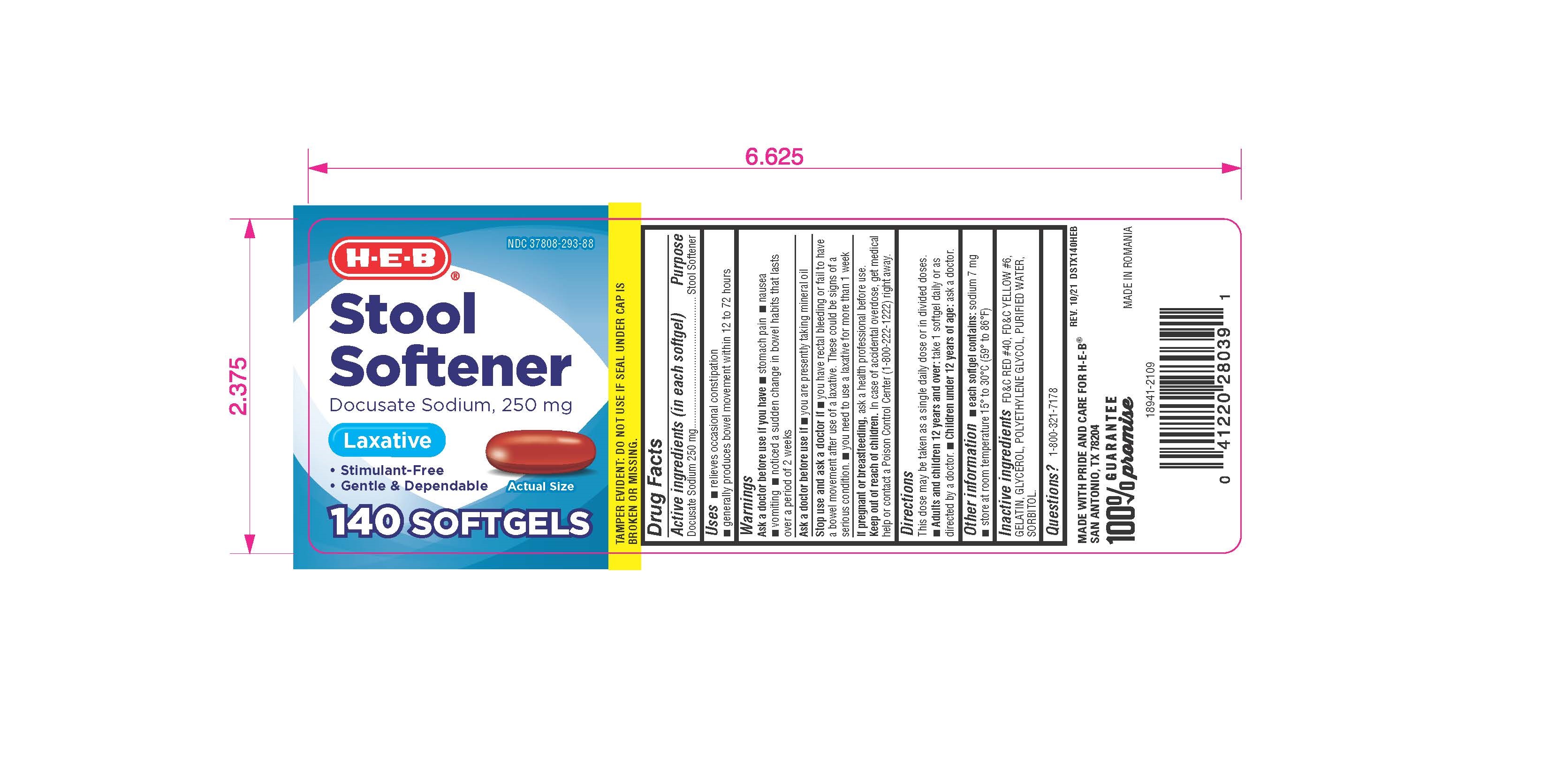 DRUG LABEL: H E B Stool Softener
NDC: 37808-293 | Form: CAPSULE, LIQUID FILLED
Manufacturer: H E B
Category: otc | Type: HUMAN OTC DRUG LABEL
Date: 20241218

ACTIVE INGREDIENTS: DOCUSATE SODIUM 250 mg/1 1
INACTIVE INGREDIENTS: FD&C RED NO. 40; FD&C YELLOW NO. 6; GELATIN; GLYCERIN; POLYETHYLENE GLYCOL, UNSPECIFIED; SORBITOL; WATER

Drug Facts

Active ingredient (in each softgel)

Docusate Sodium 250 mg

Purpose

Stool softener

Uses

- relieves occasional constipation (irregularity)
- generally produces a bowel movement in 12 to 72 hours

Warnings

Do not use

- if you are presently taking mineral oil, unless told to do so by a doctor

Ask a doctor before use if you have

- stomach pain
- nausea
- vomiting
- noticed a sudden change in bowel movements that lasts over 2 weeks

Stop use and ask a doctor if

- you have rectal bleeding or fail to have a bowel movement after use of a laxative. These could be signs of a serious condition.
- you need to use a stool softener laxative for more than 1 week

PREGNANCY OR BREAST FEEDING

If pregnant or breast-feeding, ask a health professional before use.

Keep out of reach of children. In case of overdose, get medical help or contact a Poison Control Center right away.

Directions

Take only by mouth. Doses may be taken as a single daily dose or in divided doses.

adults and children 12 years and over | take 1 to 3 softgels daily
children 2 to under 12 years of age | take 1 softgel daily
children under 2 years | ask a doctor

Other information

- each softgel contains: sodium 7 mg
- store at room temperature 15° to 30°C (59° to 86°F)

Inactive Ingredients

FD&C RED #40, FD&C YELLOW #6, GELATIN, GLYCEROL, POLYETHYLENE GLYCOL, PURIFIED WATER, SORBITOL.